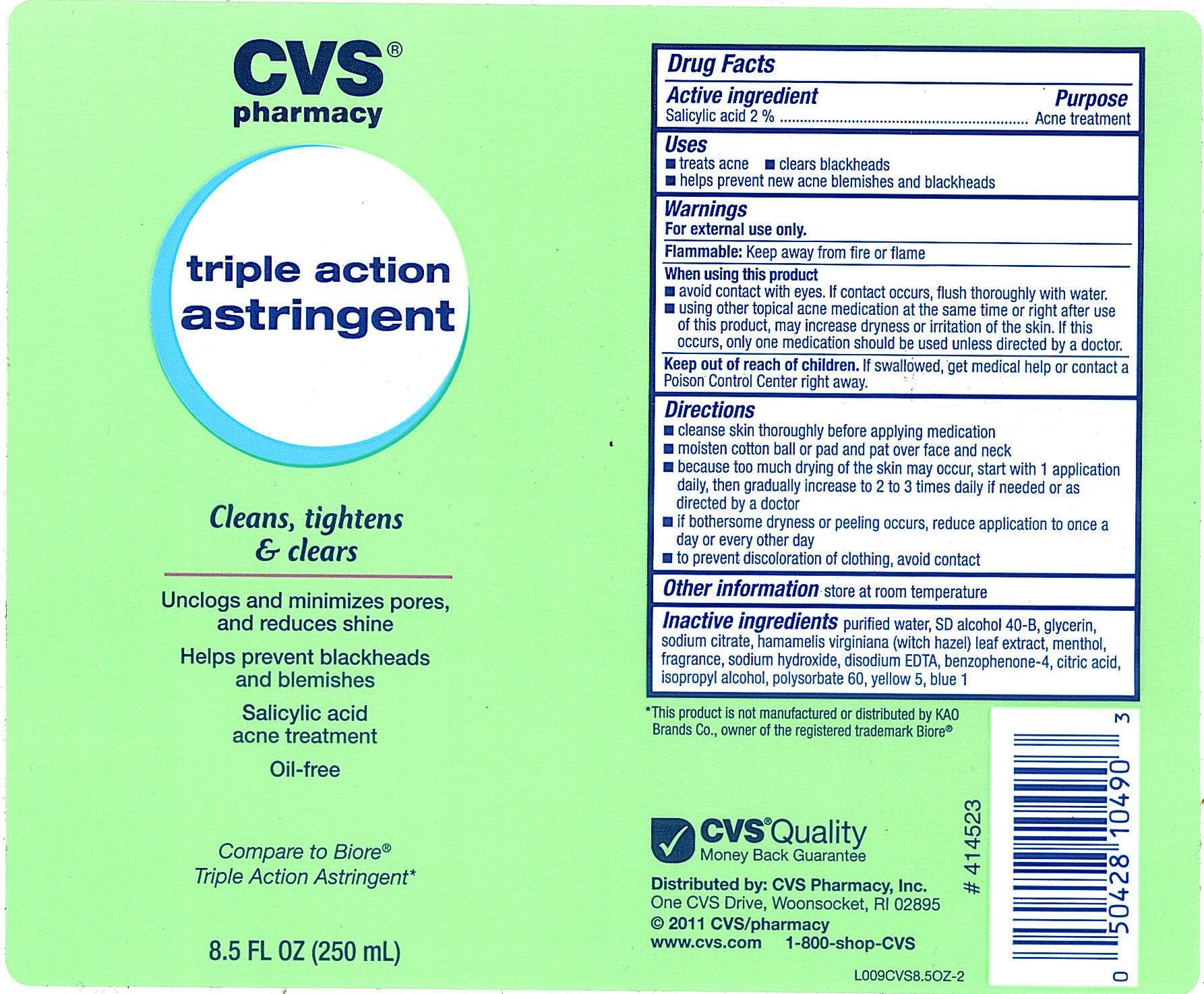 DRUG LABEL: CVS Triple Action Astringent
NDC: 59779-807 | Form: LIQUID
Manufacturer: CVS Pharmacy
Category: otc | Type: HUMAN OTC DRUG LABEL
Date: 20100708

ACTIVE INGREDIENTS: SALICYLIC ACID 20.5 mg/1 mL
INACTIVE INGREDIENTS: WATER; ALCOHOL; ISOPROPYL ALCOHOL; POLYSORBATE 60; MENTHOL; SODIUM CITRATE; BENZOPHENONE; EDETATE DISODIUM; HAMAMELIS VIRGINIANA LEAF; GLYCERIN; FD&C YELLOW NO. 5; FD&C BLUE NO. 1; SODIUM HYDROXIDE; CITRIC ACID MONOHYDRATE

drug facts

Active ingredient Purpose
Salicylic Acid..................................................Acne treatment

Uses
- treats acne - clears blackheads
- helps prevent new acne blemishes and blackheads

Keep out of reach of children. If swallowed, get medical help or contact a
Poison Control Center right away.

Uses
- treats acne - clears blackheads
- helps prevent new acne blemishes and blackheads

Warnings
For external use only
Flammable: Keep away from fire or flame
When using this product
- avoid contact with eyes. If contact occurs, flush thoroughly with water.
- using other topical acne medication at the same time or right after use of this product,
may increase dryness or irritation of the skin. If this occurs, only one medication should
be used unless directed by a doctor.
Keep out of reach of children.If swallowed, get medical help or contact a
Poison Control Center right away.

Directions
- cleanse skin thoroughly before applying medication
- moisten cotton ball or pad and pat over face and neck
- because too much drying of teh skin may occur, start with 1 application daily,
then gradually increase to 2 to 3 times daily if needed or as directed by a doctor
- if bothersome dryness or peeling occurs, reduce application to once a day or every other day
- to prevent discoloration of clothing, avoid contact

Inactive Ingredients
purified water, SD alcohol 40-B, glycerin, sodium citrate, hamamelis virginiana
(witch hazel) leaf extract, menthol, fragrance, sodium hydroxide, disodium EDTA,
benzophenone-4, citric acid, isopropyl alcohol, polysorbate 60, yellow 5 blue 1